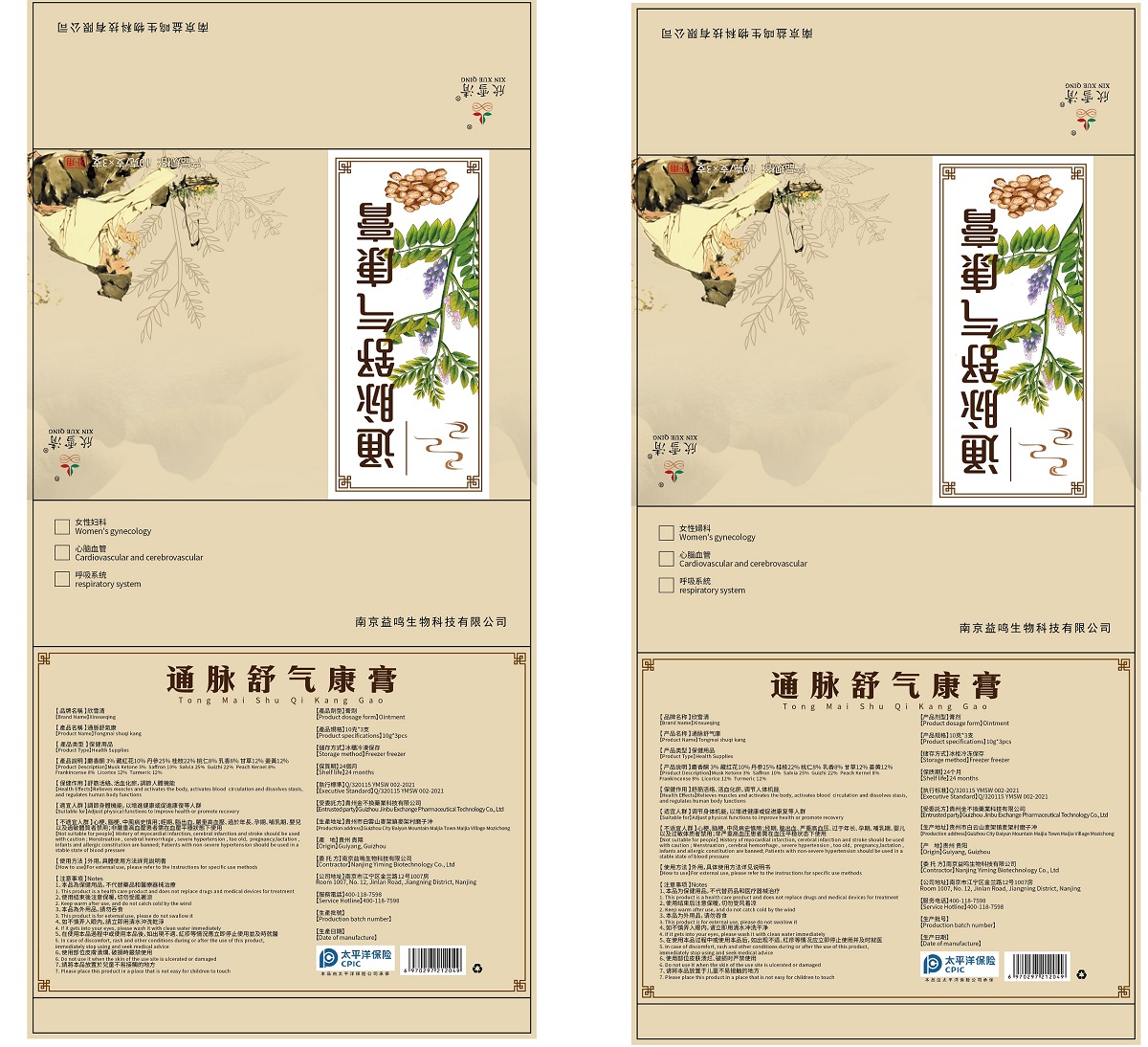 DRUG LABEL: MUSK KETONE, SAFFRON, SALVIA MILTIORRHIZA, FRANKINCENSE, LICORICE, TURMERIC
NDC: 83312-001 | Form: PASTE
Manufacturer: Nanjing Yiming Biotechnology Co., Ltd.
Category: homeopathic | Type: HUMAN OTC DRUG LABEL
Date: 20230306

ACTIVE INGREDIENTS: FRANKINCENSE 8 g/100 g; SALVIA MILTIORRHIZA WHOLE 25 g/100 g; LICORICE 12 g/100 g; MUSK KETONE 3 g/100 g; SAFFRON 10 g/100 g; TURMERIC 12 g/100 g
INACTIVE INGREDIENTS: PRUNUS PERSICA SEED; CINNAMOMUM CASSIA TWIG

Xinxueqing Tongmai Shuqi Kang

Active ingredients

Musk Ketone, Saffron, Salvia, Frankincense, Licorice, Turmeric

Purpose

Dredge channels and collaterals, promote blood circulation and remove stasis, and regulate human functions，Excellent is reflected in the human respiratory system, cardiovascular and cerebrovascular female gynecological system

KEEP OUT OF REACH OF CHILDREN

Please place this product in a place that is not easy for children to touch

Use

For external use, put this product into one side of the nostrils, and wear the head cover and foot cover to relax and lie down for normal breathing for 2 to 3 hours

Warning

1. This product is a health care product and does not replace drugs and medical devices for treatment

2. Keep warm after use, and do not catch cold by the wind

3. This product is for external use, please do not swallow it

4. If it gets into your eyes, please wash it with clean water immediately

5. In case of discomfort, rash and other conditions during or after the use of this product, immediately stop using and seek medical advice

6. Do not use it when the skin of the use site is ulcerated or damaged

7. Please place this product in a place that is not easy for children to touch

WARNINGS AND PRECAUTIONS

People with a history of myocardial infarction, cerebral infarction, and stroke should be cautious; During menstruation, patients with intracerebral hemorrhage, severe hypertension, the elderly, pregnancy, lactation, infants and allergic constitution are prohibited. Patients with non-serious hypertension should use it under stable blood pressure

DOSAGE AND ADMINISTRATION

10 grams/tube/time, use for 100 minutes to 120 minutes. One can be used twice. After the product is used for the first time, it is recommended to keep it sealed and refrigerated

Inactive ingredients

Frankincense, Guizhi